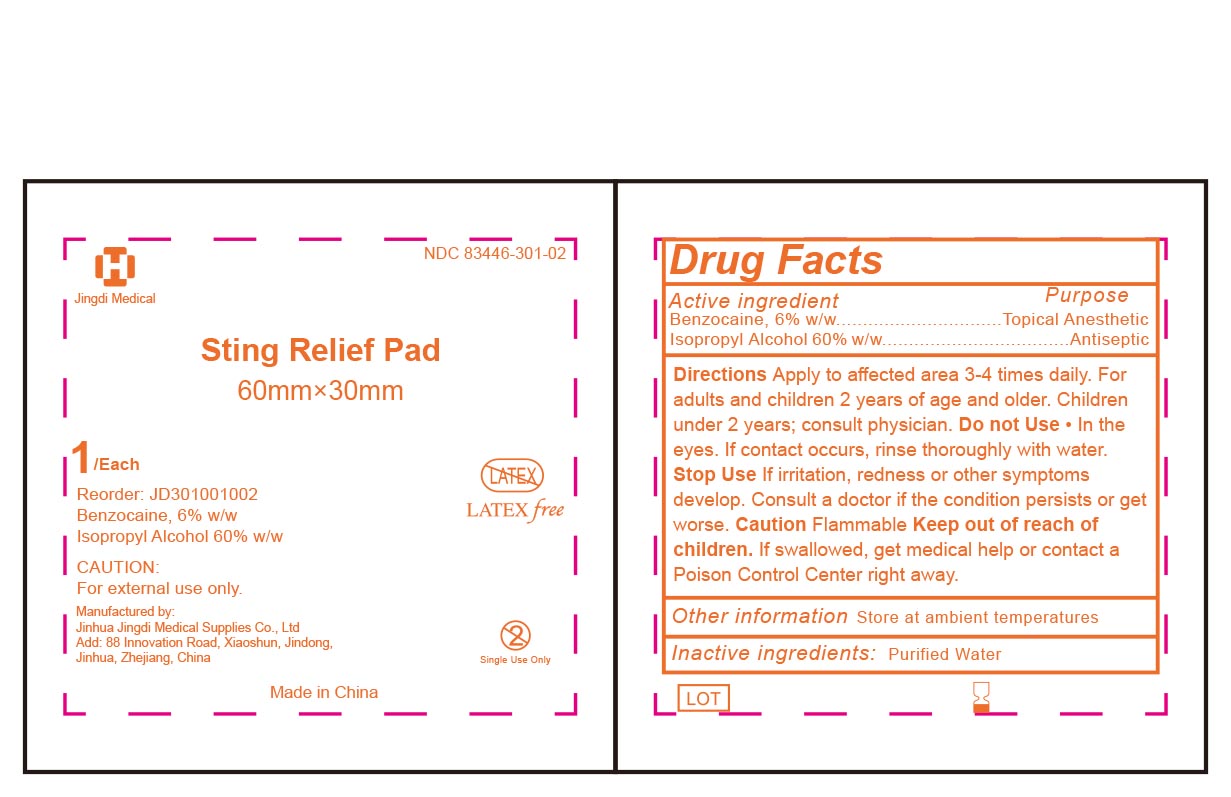 DRUG LABEL: Sting Relief Pad
NDC: 83446-301 | Form: CLOTH
Manufacturer: JINHUA JINGDI MEDICAL SUPPLIES CO., LTD
Category: otc | Type: HUMAN OTC DRUG LABEL
Date: 20260101

ACTIVE INGREDIENTS: ISOPROPYL ALCOHOL 0.6 g/1 g; BENZOCAINE 0.06 g/1 g
INACTIVE INGREDIENTS: WATER

ACTIVE INGREDIENT

Benzocaine 6.0% w/w

Isopropyl Alcohol 60% w/w

DESCRIPTION

For temporary relief of pain and itching associated with minor burns, scrapes and insect bites.

For external use only.

INACTIVE INGREDIENT

Purified water

PURPOSE

Topical Anesthetic

Antiseptic

WARNINGS

For external use only.

Caution Flammable.

Stop Use if irritation, redness or other symptoms develop. Consult a doctor if the condition persists or get worse.

Keep out of reach of children

If swallowed, get medical help or contact a Poison Control Center right away.

Directions

Apply to affected area 3-4 times daily for adults and children 2 years of age and older.

Children under 2 years consult physician.

Do not Use in the eyes.

If contact occurs, rinse thoroughtly with water.

DOSAGE AND ADMINISTRATION

Apply topically as needed to cleanse intendend area；
Apply the product to the skin, take the injection or puncture site as the center, slowly rotate from the insideto the outside, and gradually apply the product for two times, the disinfection area should be more than5cmx5cm, and the action time should be 1min.